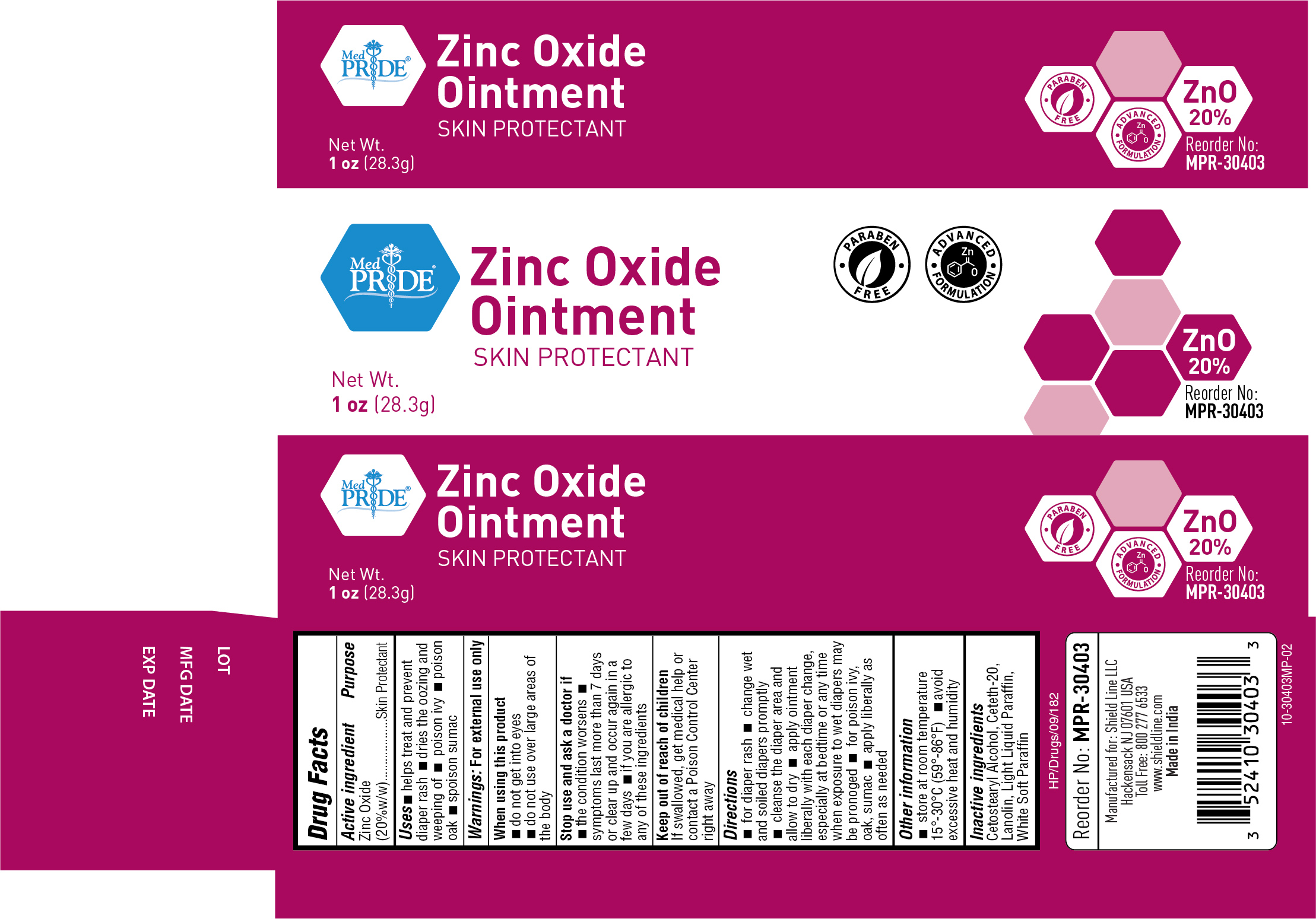 DRUG LABEL: Medpride
NDC: 52410-3040 | Form: OINTMENT
Manufacturer: Shield Line LLC
Category: otc | Type: HUMAN OTC DRUG LABEL
Date: 20250818

ACTIVE INGREDIENTS: ZINC OXIDE 20 g/100 g
INACTIVE INGREDIENTS: LANOLIN; CETOSTEARYL ALCOHOL; CETETH-20; LIGHT MINERAL OIL; PETROLATUM

MedPride Zinc oxide 20%

Active Ingredient

Zinc Oxide 20% w/w

Purpose

Skin Protectant

Uses

■ helps treat and prevent diaper rash ■ dries the oozing and weeping of ■ poison ivy ■ poison oak ■ poison sumac

Warnings

For external use only

When using this product

■ do not get into eyes

■ do not use over large areas of the body

Stop use and ask a doctor if

■ the condition worsens ■ symptoms last more than 7 days or clear up and occur again in a few days ■ if you are allergic to any of these ingredients

Keep out of reach of children. If swallowed, get medical help or contact a Poison Control Center right away

Directions

■ for diaper rash ■ change wet and soiled diapers promptly ■ cleanse the diaper area and allow to dry ■ apply ointment liberally with each diaper change, especially at bedtime or anytime when exposure to wet diapers may be prolonged ■ for poison ivy, oak sumac ■ apply ointment liberally as often as needed

Other Information

■ store at 59-86F (15-30C)

Inactive Ingredients

cetostearyl alcohol, cetomacrogol 1000, lanolin, light liquid paraffin, white soft parrafin